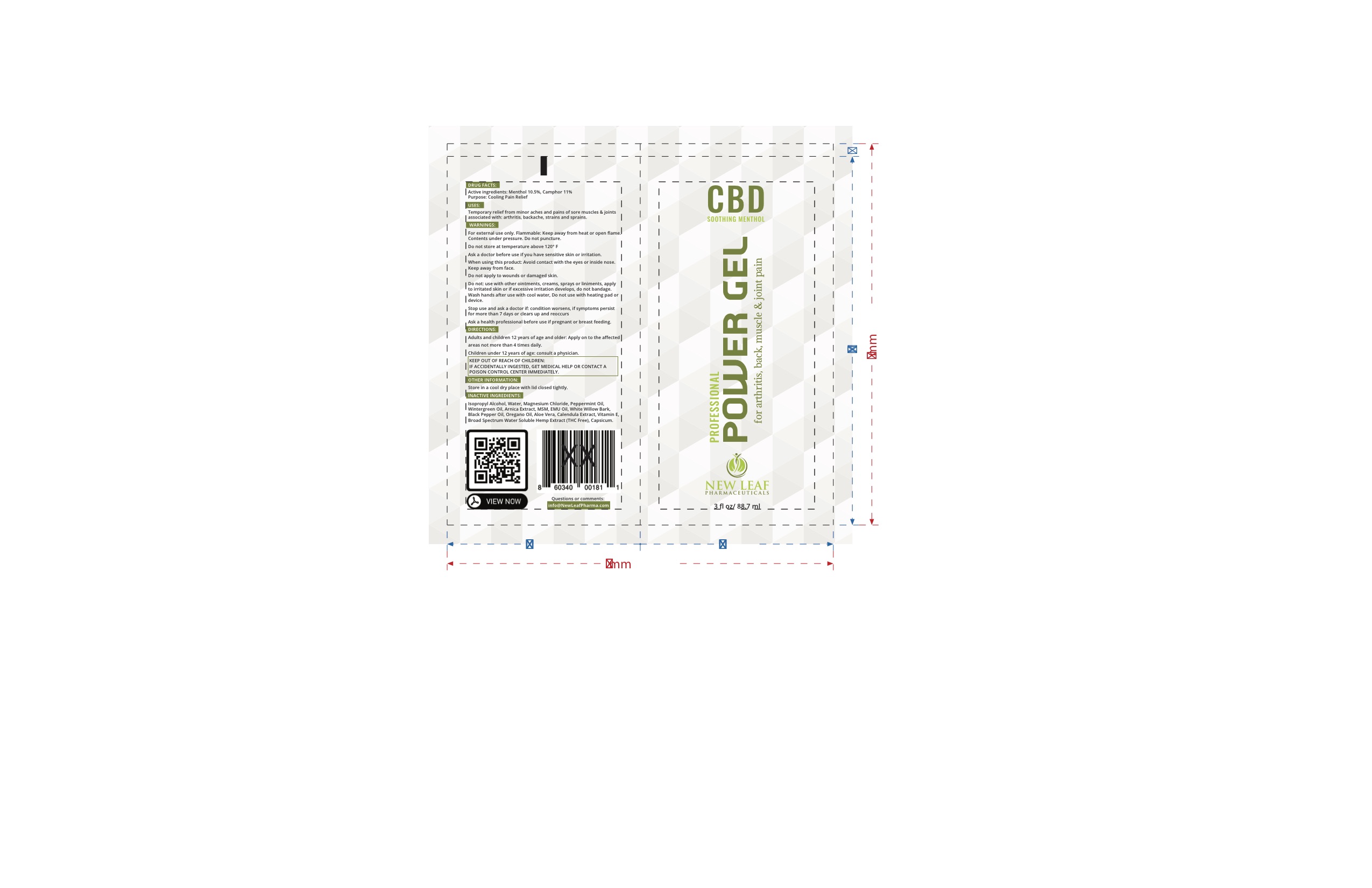 DRUG LABEL: PS
NDC: 71798-006 | Form: GEL
Manufacturer: New Leaf Pharmaceutical, LLC
Category: otc | Type: HUMAN OTC DRUG LABEL
Date: 20200124

ACTIVE INGREDIENTS: MENTHOL, UNSPECIFIED FORM 10.5 g/10.5 mL
INACTIVE INGREDIENTS: CALENDULA OFFICINALIS FLOWER; ISOPROPYL ALCOHOL; MAGNESIUM CHLORIDE; ARNICA MONTANA FLOWER WATER; WILLOW BARK; HYDROXYETHYL CELLULOSE (2000 CPS AT 1%); ALOE VERA LEAF

CBD Power Gel Professional